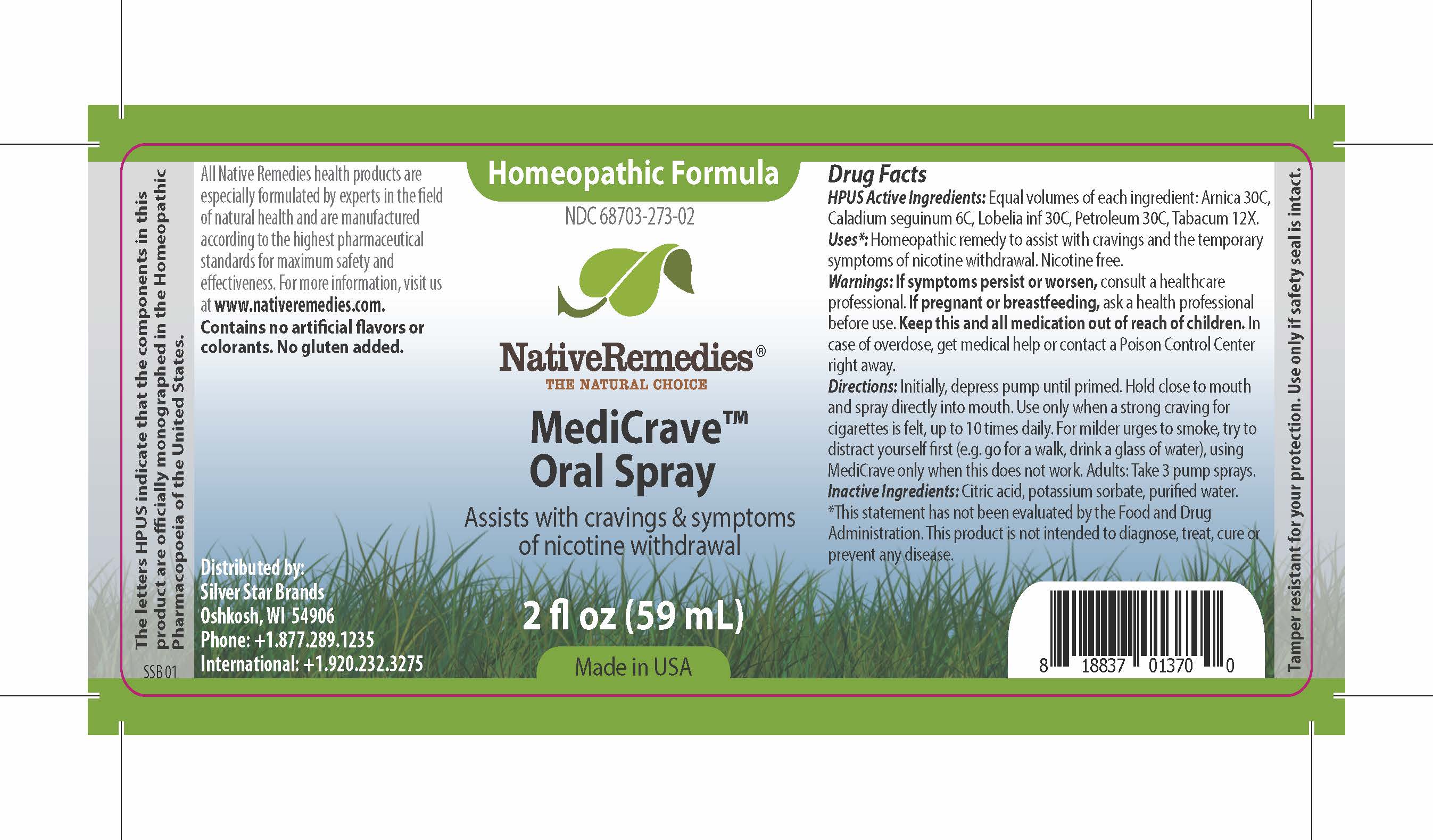 DRUG LABEL: MediCrave
NDC: 68703-273 | Form: SPRAY
Manufacturer: Silver Star Brands
Category: homeopathic | Type: HUMAN OTC DRUG LABEL
Date: 20170206

ACTIVE INGREDIENTS: ARNICA MONTANA 30 [hp_C]/59 mL; LIQUID PETROLEUM 30 [hp_C]/59 mL; DIEFFENBACHIA SEGUINE 6 [hp_C]/59 mL; LOBELIA INFLATA 30 [hp_C]/59 mL; TOBACCO LEAF 12 [hp_X]/59 mL
INACTIVE INGREDIENTS: WATER; ANHYDROUS CITRIC ACID; POTASSIUM SORBATE

NativeRemedies® MediCrave™ Oral Spray

HPUS Active Ingredients:

Equal volumes of each ingredient: Arnica 30C, Caladium seguinum 6C, Lobelia inf 30C, Petroleum 30C, Tabacum 12X.

Warnings:

If symptoms persist or worsen, consult a healthcare professional. If pregnant or breastfeeding, ask a health professional before use. Keep this and all medication out of reach of children. In case of overdose, get medical help or contact a Poison Control Center right away.

Directions:

Initially, depress pump until primed. Hold close to mouth and spray directly into mouth. Use only when a strong craving for cigarettes is felt, up to 10 times daily. For milder urges to smoke, try to distract yourself first (e.g. go for a walk, drink a glass of water), using MediCrave only when this does not work. Adults: Take 3 pump sprays.

OTHER SAFETY INFORMATION

All Native Remedies health products are especially formulated by experts in the field of natural health and are manufactured according to the highest pharmaceutical standards for maximum safety and effectiveness. For more information, visit us at www.nativeremedies.com. Contains no artificial flavors or colorants. No gluten added.

Inactive Ingredients:

Citric acid, potassium sorbate, purified water.

KEEP OUT OF REACH OF CHILDREN

Keep this and all medication out of reach of children. In case of overdose, get medical help or contact a Poison Control Center right away.

PREGNANCY OR BREAST FEEDING

If pregnant or breastfeeding, ask a health professional before use.

PURPOSE

Assists with cravings & symptoms of nicotine withdrawal.

Uses

Homeopathic remedy to assist with cravings and the temporary symptoms of nicotine withdrawal. Nicotine free.

*This statement has not been evaluated by the Food and Drug Administration. This product is not intended to diagnose, treat, cure or prevent any disease.